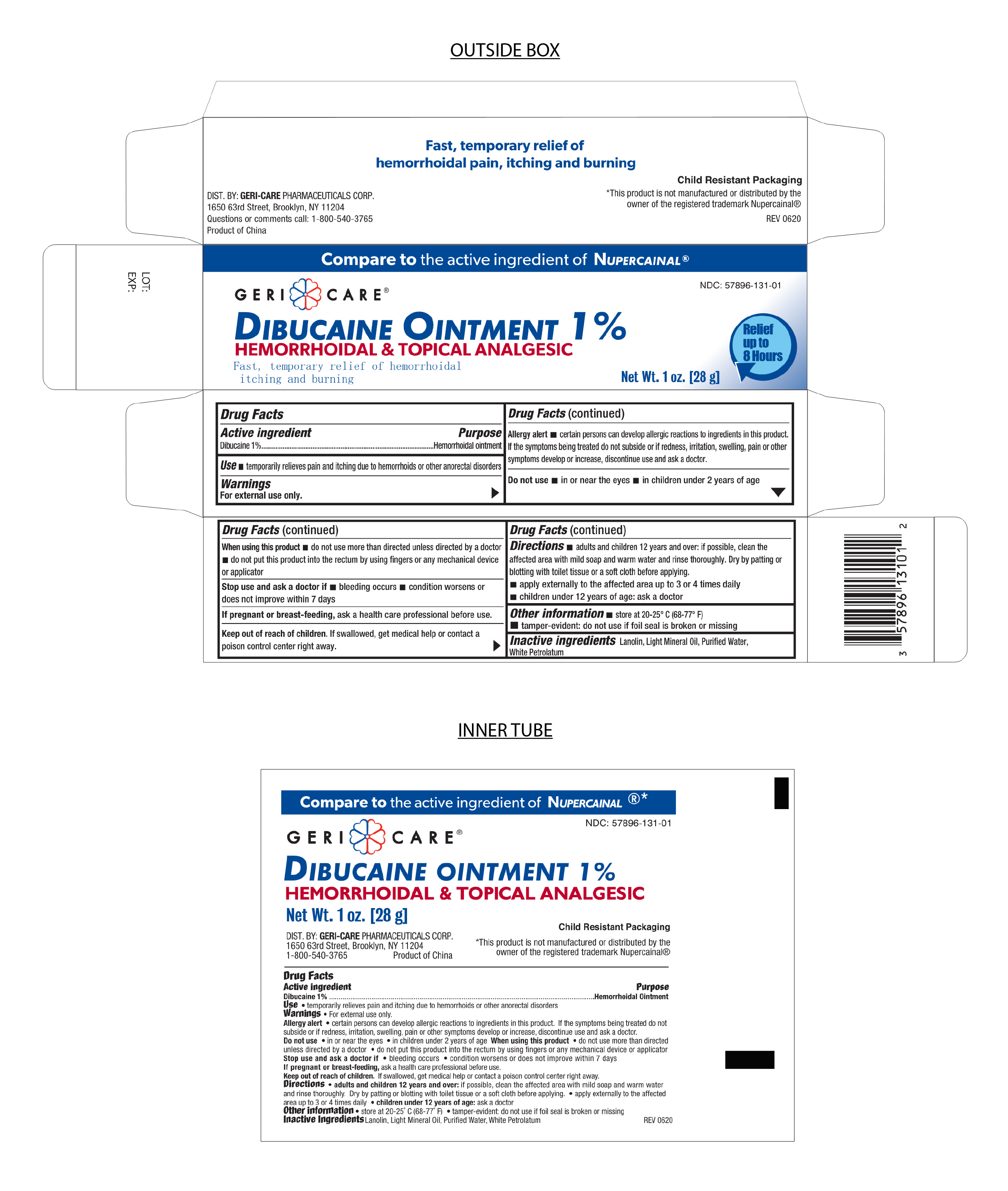 DRUG LABEL: Dibucaine
NDC: 57896-131 | Form: OINTMENT
Manufacturer: Geri-Care Pharmaceuticals, Corp
Category: otc | Type: HUMAN OTC DRUG LABEL
Date: 20241220

ACTIVE INGREDIENTS: DIBUCAINE 1 g/100 g
INACTIVE INGREDIENTS: PETROLATUM; WATER; LIGHT MINERAL OIL; LANOLIN

GERI-CARE Dibucaine Ointment 1%

Active Ingredient

Dibucaine 1%

PURPOSE

Hemorrhoidal Ointment

INDICATIONS AND USAGE

Temporarily relieves pain and itching due to hemorrhoids or other anorectal disorders.

If Pregnant or Breast-Feeding

Ask a health care professional before use.

Stop Use and ask a doctor

- Bleeding occurs
- Condition worsens or does not improve within 7 days

Keep out of the reach of Children

If swallowed, get medical help or contact a Poison Control Center right away.

Do Not Use

In or near eyes

In children under 2 years of age

Warnings

For External use only

Allergy alert

Certain persons can develop allergic reactions to ingredients in this product.

If the symptoms being treated do not subside or if redness, irritation, swelling, pain, or other symptoms develop or increase, discontinue use and ask a doctor.

When using this product

Do not use more than directed unless directed by a doctor

Do not put this product into the rectum by using fingers or any mechanical device or applicator.

Directions

- Adults and children 12 years of age or older. If possible, clean the affected area with mild soap and warm water and rinse thoroughly. Dry by patting or blotting with toilet tissue or a soft cloth before applying.
- Apply externally to the affected area up to 3 to 4 times daily.

Children under 12 years of age. ask a doctor

Other Information

- Store at 20º-25ºC (68º-77ºF)

Tamper-evident; do not use if foil seal is broken or missing

Inactive Ingredients

Lanolin, Light Mineral Oil, Purified Water, White Petrolatum

Distributed By

Geri-Care Pharmaceuticals Corp.

1650 63rd Street

Brooklyn, NY 11204

1-800-540-3765

Product of China

* This product is not manufactured or distributed by the owner of the registered trademark Nupercainal®